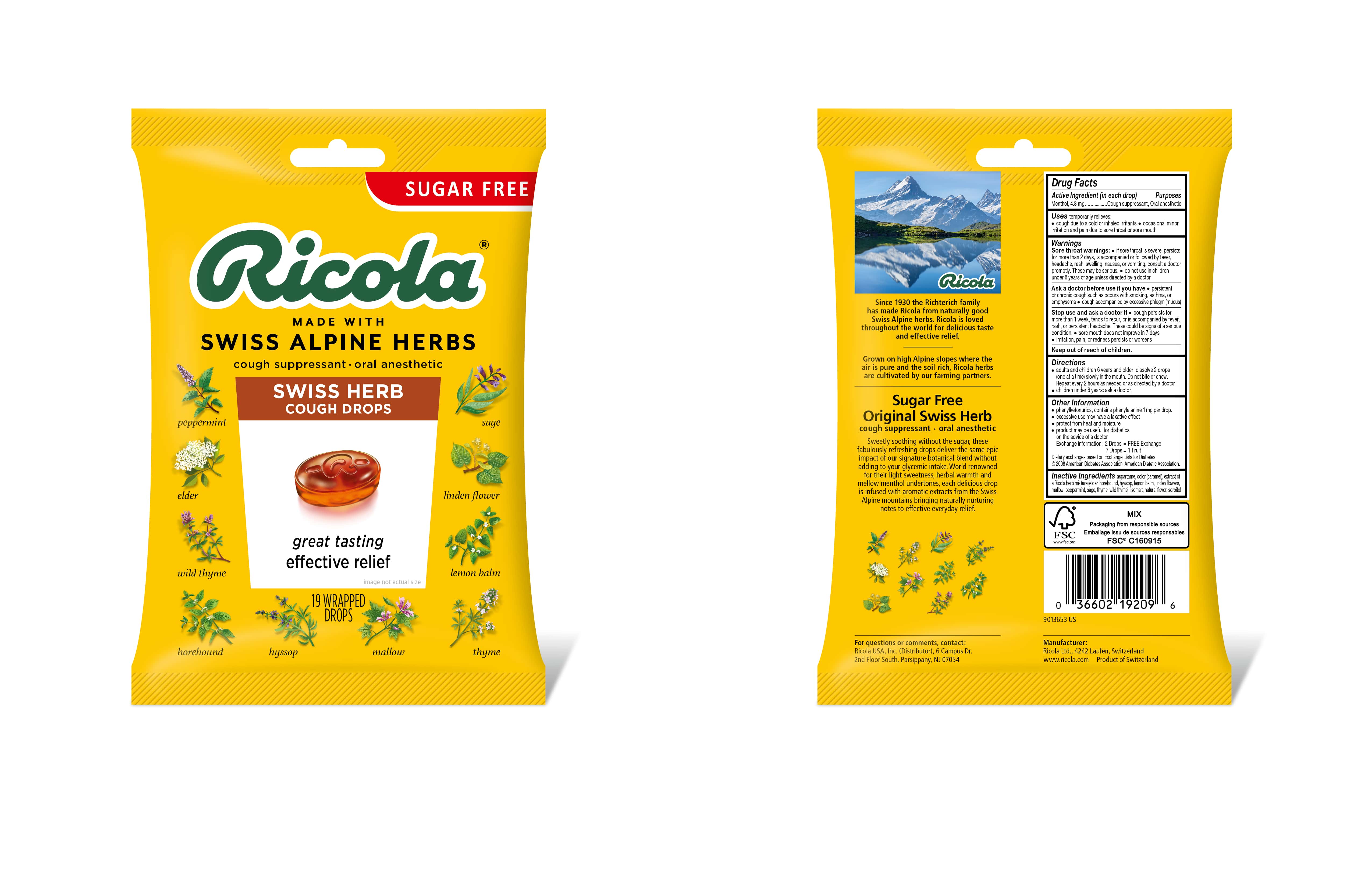 DRUG LABEL: Sugar Free Mountain Herb Cough Suppressant Throat Drops
NDC: 63667-958 | Form: LOZENGE
Manufacturer: Ricola USA Inc.
Category: otc | Type: HUMAN OTC DRUG LABEL
Date: 20241210

ACTIVE INGREDIENTS: MENTHOL 4.8 mg/1 1
INACTIVE INGREDIENTS: ISOMALT; SORBITOL; ASPARTAME; CARAMEL

ORIGINAL SWISS HERB COUGH SUPPRESSANT THROAT DROPS SUGAR FREE

Drug Facts

Purpose

Cough suppressant, Oral anesthetic

Active Ingredient (in each drop)

Menthol, 4.8 mg

Uses

temporarily relieves:

- cough due to a cold or inhaled irritants
- occasional minor irritation and pain due to sore throat or sore mouth

Warnings

Sore throat warnings:

- if sore throat is severe, persists for more than 2 days, is accompanied or followed by fever, headache, rash, swelling, nausea, or vomiting, consult a doctor promptly. These may be serious.
- do not use in children under 6 years of age unless directed by a doctor.

Ask doctor before use if you have

- persistent chronic cough such as occurs with smoking, asthma, or emphysema
- cough accompanied by excessive phlegm (mucus)

Stop use and ask a doctor if

- cough persists for more than 1 week, tends to recur, or is accompanied by fever, rash, or persistent headache. These could be signs of a serious condition.
- sore mouth does not improve in 7 days
- irritation, pain, or redness persists or worsens

Directions

- adults and children 6 years and older: dissolve 2 drops (one at a time) slowly in the mouth. Repeat every 2 hours as needed or as directed by a doctor
- children under 6 years: ask a doctor

Other Information

- Phenylketonurics: contains phenylalanine 1 mg per drop
- excessive use may have a laxative effect
- store in a dry place
- product may be useful for diabetics on the advice of a doctor

Exchange information: 2 Drops = FREE Exchange

7 Drops = 1 Fruit

Dietary exchanges based on Exchange Lists for Diabetics

© 2008 American Diabetes Association, American Dietetic Association

Inactive Ingredients

aspartame, color (caramel), extract of a Ricola herb mixture (elder, horehound, hyssop, lemon balm, linden flowers, mallow, peppermint, sage, thyme, wild thyme), isomalt, natural flavor, sorbitol